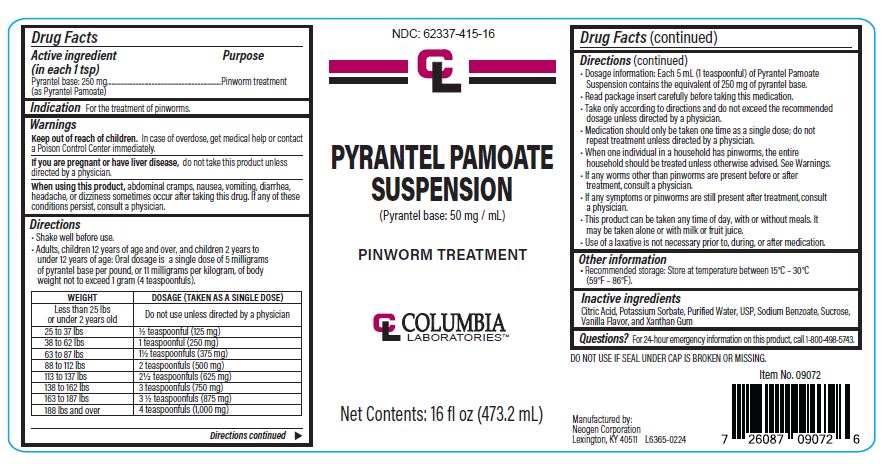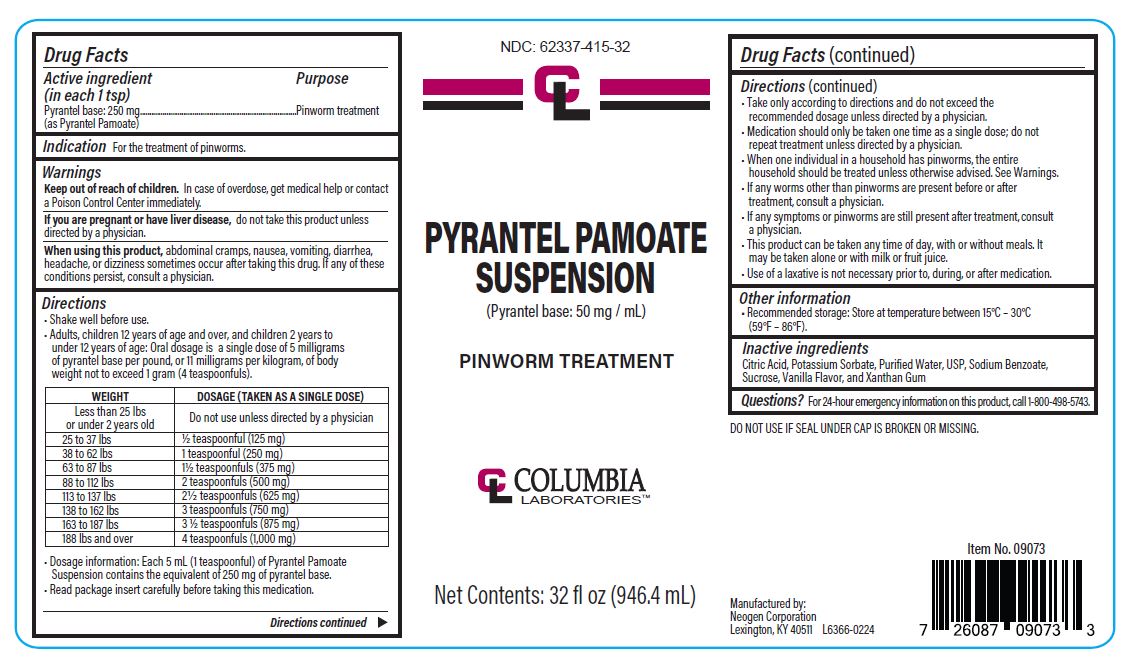 DRUG LABEL: Pyrantel Pamoate
NDC: 62337-415 | Form: SUSPENSION
Manufacturer: Neogen Corporation dba Columbia Laboratories
Category: otc | Type: HUMAN OTC DRUG LABEL
Date: 20240806

ACTIVE INGREDIENTS: PYRANTEL PAMOATE 50 mg/1 mL
INACTIVE INGREDIENTS: CITRIC ACID MONOHYDRATE; POTASSIUM SORBATE; SODIUM BENZOATE; SUCROSE; VANILLA; WATER; XANTHAN GUM

Active Ingredients (in each 1 tsp)

Pyrantel base: 250 mg

(as Pyrantel Pamoate)

Purpose

Pinworm treatment

Indication

For the treatment of pinworms.

Keep out of reach of children.In case of overdose, get medical help or contact a Poison Control Center immediately.

PREGNANCY OR BREAST FEEDING

If you are pregnant or have liver disease,do not take this product unless directed by a physician.

When using this product,abdominal cramps, nausea, vomiting, diarrhea, headache, or dizziness sometimes occur after taking this drug. If any of these conditions persist, consult a physician.

Directions

- Shake well before use.
- Adults, children 12 years of age and over, and children 2 years to under 12 years of age - oral dosage is a single dose of 5 milligrams of Pyrantel Base per pound (or 11 milligrams per kilogram) of body weight, not to exceed 1 gram (4 teaspoonfuls).

WEIGHT | DOSAGE(TAKEN AS A SINGLE DOSE)
Less than 25 Pounds or under 2 years old | Do not us unless directed by a physician
25 to 37 Pounds | ½ teaspoonful (125 mg)
38 to 62 Pounds | 1 teaspoonful (250 mg)
63 to 87 Pounds | 1½ teaspoonfuls (375 mg)
88 to 112 Pounds | 2 teaspoonfuls (500 mg)
113 to 137 Pounds | 2½ teaspoonfuls (625 mg)
138 to 162 Pounds | 3 teaspoonfuls (750 mg)
163 to 187 Pounds | 3½ teaspoonfuls (875 mg)
188 Pounds and over | 4 teaspoonfuls (1000 mg)

- Dosage information: Each 5 mL (1 teaspoonful) of Pyrantel Pamoate Suspension contains the equivalent of 250 mg of Pyrantel Base.
- Read package insert carefully before taking this medication.
- Take only according to directions and do not exceed the recommended dosage unless directed by a physician.
- Medication should only be taken one time as a single dose, do not repeat treatment - unless directed by a physician.
- When one individual in a household has pinworms, the entire household should be treated unless otherwise advised.
- If any worms other than pinworms are present before or after treatment, consult a physician.
- If any symptoms or pinworms are still present after treatment, consult a physician.
- This product can be taken any time of day, with or without meals. It may be taken alone or with milk or fruit juice.
- Use of a laxative is not necessary prior to, during, or after medication.

Other information

- Recommended storage: Store at temperature between 15°C - 30°C (59°F - 86°F).

Inactive Ingredients

Citric Acid, Potassium Sorbate, Purified Water, USP, Sodium Benzoate, Sucrose, Vanilla Flavor, and Xanthan Gum

Questions?

For 24-hour emergency information on this product, call 1-800-498-5743.

DO NOT USE IF SEAL UNDER CAP IS BROKEN OR MISSING.

PYRANTEL PAMOATE ORAL SUSPENSION USP (Pyrantel base: 50 mg / mL) PINWORM TREATMENT

Drug Facts

Active ingredient

(in each 1 tsp)

Pyrantel base: 250 mg

(as Pyrantel Pamoate)

Purpose

Pinworm treatment

Indication For the treatment of pinworms.

Warnings

Keep out of reach of children.In case of overdose, get medical help or contact a Poison Control Center immediately.

If you are pregnant or have liver disease,do not take this product unless directed by a physician.

When using this product,abdominal cramps, nausea, vomiting, diarrhea, headache, or dizziness sometimes occur after taking this drug. If any of these conditions persist, consult a physician.

Directions

- Shake well before use.
- Adults, children 12 years of age and over, and children 2 years to under 12 years of age - oral dosage is a single dose of 5 milligrams of Pyrantel Base per pound (or 11 milligrams per kilogram) of body weight, not to exceed 1 gram (4 teaspoonfuls).

WEIGHT | DOSAGE (TAKEN AS A SINGLE DOSE)
Less than 25 Pounds or under 2 years old | Do not us unless directed by a physician
25 to 37 Pounds | ½ teaspoonful (125 mg)
38 to 62 Pounds | 1 teaspoonful (250 mg)
63 to 87 Pounds | 1½ teaspoonfuls (375 mg)
88 to 112 Pounds | 2 teaspoonfuls (500 mg)
113 to 137 Pounds | 2½ teaspoonfuls (625 mg)
138 to 162 Pounds | 3 teaspoonfuls (750 mg)
163 to 187 Pounds | 3½ teaspoonfuls (875 mg)
188 Pounds and over | 4 teaspoonfuls (1000 mg)

- Dosage information: Each 5 mL (1 teaspoonful) of Pyrantel Pamoate Suspension contains the equivalent of 250 mg of Pyrantel Base.
- Read package insert carefully before taking this medication.
- Take only according to directions and do not exceed the recommended dosage unless directed by a physician.
- Medication should only be taken one time as a single dose, do not repeat treatment - unless directed by a physician.
- When one individual in a household has pinworms, the entire household should be treated unless otherwise advised.
- If any worms other than pinworms are present before or after treatment, consult a physician.
- If any symptoms or pinworms are still present after treatment, consult a physician.
- This product can be taken any time of day, with or without meals. It may be taken alone or with milk or fruit juice.
- Use of a laxative is not necessary prior to, during, or after medication.

Other information

- Recommended storage: Store at temperature between 15°C - 30°C (59°F - 86°F).

Inactive Ingredients

Citric Acid, Potassium Sorbate, Purified Water, USP, Sodium Benzoate, Sucrose, Vanilla Flavor, and Xanthan Gum

Questions?Call 859-254-1221 or toll-free 800-621-8829.

PYRANTEL PAMOATE

READ THIS INSERT THOROUGHLY BEFORE TAKING THIS PRODUCT.

This brochure will tell you about pinworms and how to treat infections effectively with Pyrantel Pamoate. Many who have pinworms do not have symptoms. Nevertheless, many will experience itching in and around the rectal opening. The itching may be very annoying and continued scratching can cause an irritation in this area. The itching may be presented at night when sleeping. That is why restless sleep is sometimes a sign of pinworms, especially in children. It is important for you to realize that you should only treat with Pyrantel Pamoate if you have seen and identified the pinworms.

Pinworms look like tiny white threads. The female pinworm is about ½ long (the male pinworm is shorter). They live in the bowel. Usually, at night, the female travels to the rectal opening and lays eggs within the skin folds around the opening. This usually takes place within one to two hours after the child has been put to bed for the night. The sticky gelatin-like substance in which the eggs (they are too small to see) are deposited and the movement of the female pinworm may cause annoying itching and possibly restless sleep. By checking the rectal opening at this time, you can attempt to see the pinworm as described.

The pinworm eggs normally survive for as long as three weeks. In that time, the pinworm egg may hatch and the pinworm will travel back within the rectal opening into the bowel. The pinworm reaches maturity in the bowel within two to six weeks and the life cycle repeats itself.

Scratching will cause pinworm eggs to stick to the fingers. Reinfection will result if the fingers are placed in the mouth. The eggs, which are too small to see, contaminate whatever they come in contact with: bed clothes, underwear, toys, hands, and food touched by contaminated hands. Even eggs floating in the air can be swallowed and cause infection. Eggs deposited in the environment, as stated above, can survive for as long as three weeks. Pinworms are highly contagious. Even the cleanest and most careful people can get them.

After treatment with Pyrantel Pamoate, there are some rules to follow to try to prevent spreading to others and reinfection:

- Wash hands and fingernails with soap often during the day, especially before eating and after using the toilet.
- Wear tight underpants both day and night. Change them daily.
- For several days after treatment, clean the bedroom floor by vacuuming or damp mopping. Avoid dry sweeping that may stir up dust.
- After treatment, wash bed linens and night clothes (don't shake them).
- Keep the toilet seats clean.

Colombia Laboratories

944 Nandino Blvd.

Lexington, KY 40511

PACKAGE LABEL

NDC: 62337-415-16

PYRANTEL PAMOATE SUSPENSION

(Pyrantel base: 50 mg / mL)

PINWORM TREATMENT

COLOMBIA LABORATORIES

944 Nandino Blvd.

Lexington, KY 40511

NET CONTENTS:16 FL OZ (473.2 mL)

PACKAGE LABEL

NDC: 62337-415-32

PYRANTEL PAMOATE SUSPENSION

(Pyrantel base: 50 mg / mL)

PINWORM TREATMENT

COLOMBIA LABORATORIES

944 Nandino Blvd.

Lexington, KY 40511

NET CONTENTS:32 FL OZ (946.4 mL)